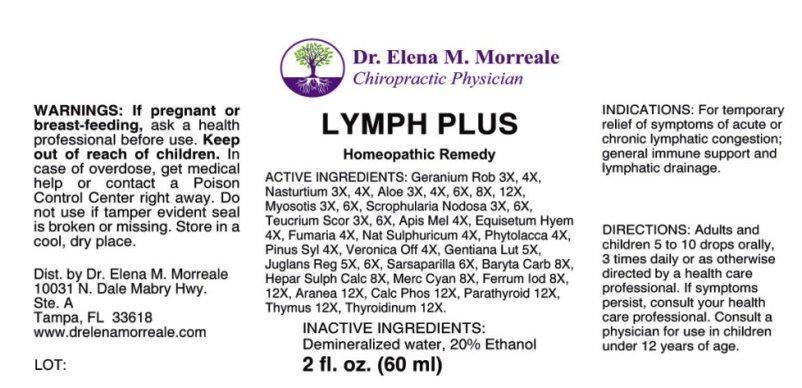 DRUG LABEL: Lymph Plus
NDC: 50813-0007 | Form: LIQUID
Manufacturer: Dr. Elena M. Morreale
Category: homeopathic | Type: HUMAN OTC DRUG LABEL
Date: 20150121

ACTIVE INGREDIENTS: GERANIUM ROBERTIANUM 3 [hp_X]/1 mL; NASTURTIUM AQUATICUM 3 [hp_X]/1 mL; ALOE 3 [hp_X]/1 mL; MYOSOTIS ARVENSIS 3 [hp_X]/1 mL; SCROPHULARIA NODOSA 3 [hp_X]/1 mL; TEUCRIUM SCORODONIA FLOWERING TOP 3 [hp_X]/1 mL; APIS MELLIFERA 4 [hp_X]/1 mL; EQUISETUM HYEMALE 4 [hp_X]/1 mL; FUMARIA OFFICINALIS FLOWERING TOP 4 [hp_X]/1 mL; SODIUM SULFATE 4 [hp_X]/1 mL; PHYTOLACCA AMERICANA ROOT 4 [hp_X]/1 mL; PINUS SYLVESTRIS LEAFY TWIG 4 [hp_X]/1 mL; VERONICA OFFICINALIS FLOWERING TOP 4 [hp_X]/1 mL; GENTIANA LUTEA ROOT 5 [hp_X]/1 mL; JUGLANS REGIA LEAF 5 [hp_X]/1 mL; JUGLANS REGIA FRUIT RIND, IMMATURE 5 [hp_X]/1 mL; SARSAPARILLA 6 [hp_X]/1 mL; BARIUM CARBONATE 8 [hp_X]/1 mL; CALCIUM SULFIDE 8 [hp_X]/1 mL; MERCURIC CYANIDE 8 [hp_X]/1 mL; FERROUS IODIDE 8 [hp_X]/1 mL; ARANEUS DIADEMATUS 12 [hp_X]/1 mL; TRIBASIC CALCIUM PHOSPHATE 12 [hp_X]/1 mL; BOS TAURUS PARATHYROID GLAND 12 [hp_X]/1 mL; SUS SCROFA THYMUS 12 [hp_X]/1 mL; SUS SCROFA THYROID 12 [hp_X]/1 mL
INACTIVE INGREDIENTS: WATER; ALCOHOL

Drug Facts:

ACTIVE INGREDIENTS:

Geranium robertianum 3X, 4X, Nasturtium aquaticum 3X, 4X, Aloe socotrina 3X, 4X, 6X, 8X, 12X, Myosotis arvensis 3X, 6X, Scrophularia nodosa 3X, 6X, Teucrium scorodonia 3X, 6X, Apis mellifica 4X, Equisetum hyemale 4X, Fumaria officinalis 4X, Natrum sulphuricum 4X, Phytolacca decandra 4X, Pinus sylvestris 4X, Veronica officinalis 4X, Gentiana lutea 5X, Juglans regia 5X, 6X, Sarsaparilla 6X, Baryta carbonica 8X, Hepar sulphuris calcareum 8X, Mercurius cyanatus 8X, Ferrum iodatum, 8X, 12X, Aranea diadema 12X, Calcarea phosphorica 12X, Parathyroid (Bovine) 12X, Thymus (Suis) 12X, Thyroidinum (Suis) 12X.

INDICATIONS:

For temporary relief of symptoms of acute or chronic lymphatic congestion; general immune support and lymphatic drainage.

WARNINGS:

If pregnant or breast-feeding, ask a health professional before use.

Keep out of reach of children. In case of overdose, get medical help or contact a Poison Control Center right away.

Do not use if tamper evident seal is broken or missing.

Store in a cool, dry place.

Keep out of reach of children. In case of overdose, get medical help or contact a Poison Control Center right away.

DIRECTIONS:

Adults and children 5 to 10 drops orally, 3 times daily or as otherwise directed by a health care professional. If symptoms persist, consult your health care professional. Consult a physician for use in children under 12 years of age.

INDICATIONS:

For temporary relief of symptoms of acute or chronic lymphatic congestion; general immune support and lymphatic drainage.

INACTIVE INGREDIENTS:

Demineralized water, 20% Ethanol

QUESTIONS:

Dist. by Dr. Elena M. Morreale

10031 N. Dale Mabry Hwy.

Ste. A

Tampa, FL 33618

www.drelenamorreale.com

PACKAGE LABEL DISPLAY:

Dr. Elena M. Morreale

Chiropractic Physician

LYMPH PLUS

Homeopathic Remedy

2 fl. oz. (60 ml)